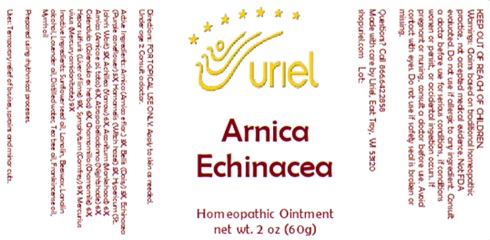 DRUG LABEL: Arnica Echinacea
NDC: 48951-1406 | Form: OINTMENT
Manufacturer: Uriel Pharmacy, Inc
Category: homeopathic | Type: HUMAN OTC DRUG LABEL
Date: 20250908

ACTIVE INGREDIENTS: ATROPA BELLADONNA 6 [hp_X]/1 g; HAMAMELIS VIRGINIANA TOP 5 [hp_X]/1 g; ARNICA MONTANA 6 [hp_X]/1 g; BELLIS PERENNIS 5 [hp_X]/1 g; ARNICA MONTANA FLOWER 3 [hp_X]/1 g; CHAMOMILE 6 [hp_X]/1 g; ACONITUM NAPELLUS 6 [hp_X]/1 g; CALCIUM SULFIDE 9 [hp_X]/1 g; ST. JOHN'S WORT 5 [hp_X]/1 g; MERCURY 9 [hp_X]/1 g; ACHILLEA MILLEFOLIUM 6 [hp_X]/1 g; CALENDULA OFFICINALIS FLOWERING TOP 6 [hp_X]/1 g; COMFREY ROOT 9 [hp_X]/1 g; ECHINACEA, UNSPECIFIED 5 [hp_X]/1 g
INACTIVE INGREDIENTS: LAVENDER OIL; TEA TREE OIL; BEESWAX; FRANKINCENSE OIL; LANOLIN ALCOHOLS; MYRRH OIL; LANOLIN; WATER; SUNFLOWER OIL

Arnica Echinacea

INDICATIONS AND USAGE

Directions: FOR TOPICAL USE ONLY.

DOSAGE AND ADMINISTRATION

Apply to skin as needed.
Under age 2: Consult a doctor.

ACTIVE INGREDIENT

Active Ingredients: Arnica (Arnica e flor.) 3X, Bellis (Daisy) 5X, Echinacea (Purple coneflower) 5X, Hamamelis (Witch hazel) 5X, Hypericum (St. John’s Wort) 5X, Achillea (Yarrow) 6X, Aconitum (Monkshood) 6X, Arnica (Arnica e pl. tota) 6X, Atropa belladonna (Nightshade) 6X, Calendula (Calendula ex herba) 6X, Chamomilla (Chamomile) 6X, Hepar sulfuris (Liver of lime) 9X, Symphytum (Comfrey) 9X, Mercurius vivus (Mercury amidonitrate) 9X

INACTIVE INGREDIENT

Inactive Ingredients: Sunflower seed oil, Lanolin, Beeswax, Lanolin alcohol, Lavender oil, Distilled water, Tea tree oil, Frankincense oil, Myrrh oil

Prepared using rhythmical processes.

PURPOSE

Uses: Temporary relief of bruises, sprains and minor cuts.

KEEP OUT OF REACH OF CHILDREN.

WARNINGS

Warnings: Claims based on traditional homeopathic practice, not accepted medical evidence. Not FDA evaluated. Do not use if allergic to any ingredient. Consult a doctor before use for serious conditions, if conditions worsen or persist, or accidental ingestion occurs. If pregnant or nursing, consult a doctor before use. Avoid contact with eyes. Do not use if safety seal is broken or missing.

Questions? Call 866.642.2858
Made with care by Uriel, East Troy, WI 53120
shopuriel.com Lot: